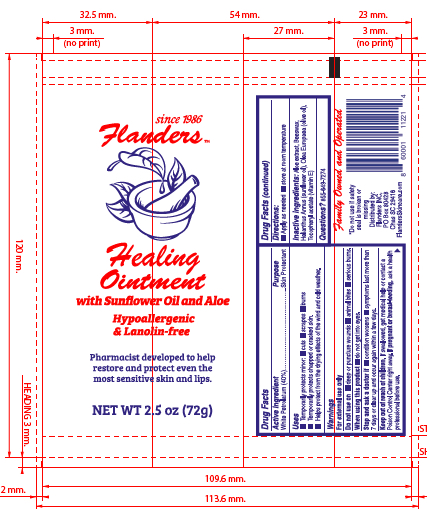 DRUG LABEL: Flanders Healing
NDC: 54323-103 | Form: OINTMENT
Manufacturer: Flanders Inc
Category: otc | Type: HUMAN OTC DRUG LABEL
Date: 20231019

ACTIVE INGREDIENTS: PETROLATUM 40 g/100 g
INACTIVE INGREDIENTS: OLIVE OIL; ALOE VERA LEAF; .ALPHA.-TOCOPHEROL ACETATE; SUNFLOWER OIL; PEG-8 BEESWAX

Active Ingredient

White Petrolatum(40%)

Uses:

- Temporarily protects minor: Cuts, scrapes and burns
- Temporarily protects chapped or cracked skin.
- Helps protect from the drying effects of wind and cold weather.

Do not use on

- Deep or puncture wounds
- animal bites
- serious burns

When using this product:

Do not get into eyes

Stop and ask a doctor if:

- Condition worsens
- Symptoms last more than 7 days or clear up and occur again within a few days.

Keep out of reach of children

If swallowed, get medical help or contact a Poison Control Center right away.

If pregnant or breast-feeding

Ask a health care professional before use.

Directions:

- Apply as needed

Inactive Ingredients:

Aloe extract, Beeswax, Helianthus Annus (sunflower oil), Olea Europea (olive oil), Tocopheryl acetate (Vitamin E)

Questions?

855-649-7274